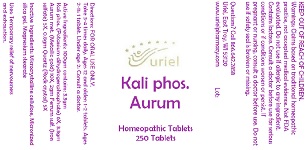 DRUG LABEL: Kali phos. Aurum
NDC: 48951-6011 | Form: TABLET
Manufacturer: Uriel Pharmacy Inc.
Category: homeopathic | Type: HUMAN OTC DRUG LABEL
Date: 20191017

ACTIVE INGREDIENTS: SILICON DIOXIDE 5 [hp_X]/1 1; POTASSIUM PHOSPHATE, MONOBASIC 6 [hp_X]/1 1; GOLD 10 [hp_X]/1 1; FERROUS SULFATE 5 [hp_X]/1 1
INACTIVE INGREDIENTS: MICROCRYSTALLINE CELLULOSE; MAGNESIUM STEARATE

Kali phos. Aurum

INDICATIONS AND USAGE

Directions: FOR ORAL USE ONLY.

DOSAGE AND ADMINISTRATION

Take 3-4 times daily. Ages 12 and older: 1-2 tablets. Ages 2-11: 1 tablet. Under age 2: Consult a doctor.

ACTIVE INGREDIENT

Active Ingredients: 100gm contains: 3.3gm Kali phos. (Potassium dihydrogenphosphate) 6X, 3.3gm Aurum met. (Metallic gold) 10X, 2gm Ferrum sulf. (Iron sulfate) 5X, 0.8gm Quartz (Rock crystal) 5X

INACTIVE INGREDIENT

Inactive Ingredients: Microcrystalline cellulose, Micronized silica gel, Magnesium stearate

PURPOSE

Uses: Temporary relief of nervousness and exhaustion.

KEEP OUT OF REACH OF CHILDREN.

WARNINGS

Warnings: Claims based on traditional homeopathic practice, not accepted medical evidence. Not FDA evaluated. Do not use if allergic to any ingredient. Contains lactose. Consult a doctor before use for serious conditions or if conditions worsen or persist. If pregnant or nursing, consult a doctor before use. Do not use if safety seal is broken or missing.

QUESTIONS

Questions? Call 866.642.2858 Uriel, East Troy, WI 53120 www.urielpharmacy.com